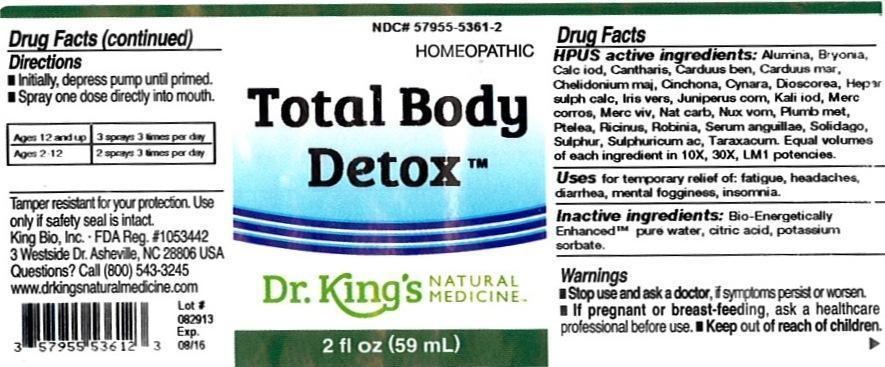 DRUG LABEL: Total Body Detox
NDC: 57955-5361 | Form: LIQUID
Manufacturer: King Bio Inc.
Category: homeopathic | Type: HUMAN OTC DRUG LABEL
Date: 20191106

ACTIVE INGREDIENTS: ALUMINUM OXIDE 10 [hp_X]/59 mL; BRYONIA ALBA ROOT 10 [hp_X]/59 mL; CALCIUM IODIDE 10 [hp_X]/59 mL; LYTTA VESICATORIA 10 [hp_X]/59 mL; CENTAUREA BENEDICTA 10 [hp_X]/59 mL; SILYBUM MARIANUM SEED 10 [hp_X]/59 mL; CHELIDONIUM MAJUS 10 [hp_X]/59 mL; CINCHONA OFFICINALIS BARK 10 [hp_X]/59 mL; CYNARA SCOLYMUS LEAF 10 [hp_X]/59 mL; DIOSCOREA VILLOSA TUBER 10 [hp_X]/59 mL; CALCIUM SULFIDE 10 [hp_X]/59 mL; IRIS VERSICOLOR ROOT 10 [hp_X]/59 mL; JUNIPER BERRY 10 [hp_X]/59 mL; POTASSIUM IODIDE 10 [hp_X]/59 mL; MERCURY 10 [hp_X]/59 mL; MERCURIC CHLORIDE 10 [hp_X]/59 mL; SODIUM CARBONATE 10 [hp_X]/59 mL; STRYCHNOS NUX-VOMICA SEED 10 [hp_X]/59 mL; LEAD 10 [hp_X]/59 mL; PTELEA TRIFOLIATA BARK 10 [hp_X]/59 mL; RICINUS COMMUNIS SEED 10 [hp_X]/59 mL; ROBINIA PSEUDOACACIA BARK 10 [hp_X]/59 mL; ANGUILLA ROSTRATA BLOOD SERUM 10 [hp_X]/59 mL; SOLIDAGO VIRGAUREA FLOWERING TOP 10 [hp_X]/59 mL; SULFUR 10 [hp_X]/59 mL; SULFURIC ACID 10 [hp_X]/59 mL; TARAXACUM OFFICINALE 10 [hp_X]/59 mL
INACTIVE INGREDIENTS: WATER; REBAUDIOSIDE A; CARYA OVATA BARK; CITRUS BIOFLAVONOIDS; LONICERA JAPONICA FLOWER; POLYEPSILON-LYSINE (4000 MW)

Total Body Detox

Drug Facts

___________________________________________________________________________________________________________________

HPUS active ingredients: Alumina, Bryonia, Calcarea iodata, Cantharis, Carduus benedictus, Carduus marianus, Chelidonium majus, Cinchona officinalis, Cynara scolymus, Dioscorea villosa, Hepar sulphuris calcareum, Iris versicolor, Juniperus communis, Kali iodatum, Mercurius corrosivus, Mercurius vivus, Natrum carbonicum, Nux vomica, Plumbum metallicum, Ptelea trifoliata, Ricinus communis, Robinia pseudoacacia, Serum anguillae, Solidago virgaurea, Sulphur, Sulphuricum acidum, Taraxacum officinale. Equal volumes of each ingredient in 10X, 30X, 1LM potencies.

INDICATIONS AND USAGE

Uses for temporary relief of: fatigue, headaches, diarrhea, mental fogginess, insomnia and indigestion.

INACTIVE INGREDIENT

Inactive ingredients: Bio-Energetically Enhanced™ pure water, carya ovata bark extract, citrus extract, lonicera japonica, polylysine, steviol glycosides.

Warnings

- Stop use and ask your doctor if symptoms persist or worsen.
- If pregnant or breast-feeding, ask a healthcare professional before use.

- Keep out of reach of children.

Directions

- Initially, depress pump until primed.
- Spray one dose directly into mouth.

Ages 12 and up: 3 sprays 3 times per day.

Ages 2-12: 2 sprays 3 times per day.

OTHER SAFETY INFORMATION

Tamper resistant for your protection. Use only if safety seal is intact.

PURPOSE

Uses for temporary relief of:

- fatigue
- headaches
- diarrhea
- mental fogginess
- insomnia.